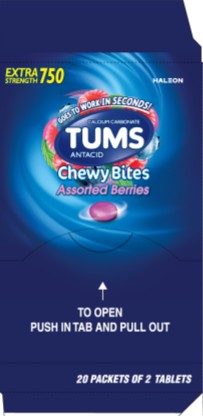 DRUG LABEL: Tums Chewy Bites
NDC: 85237-1860 | Form: TABLET, CHEWABLE
Manufacturer: Select Consumer Group
Category: otc | Type: HUMAN OTC DRUG LABEL
Date: 20251227

ACTIVE INGREDIENTS: CALCIUM CARBONATE 750 mg/1 1
INACTIVE INGREDIENTS: ACACIA; ALCOHOL; AMMONIA; YELLOW WAX; MEDIUM-CHAIN TRIGLYCERIDES; CARMINIC ACID; CARNAUBA WAX; CITRIC ACID MONOHYDRATE; COCONUT OIL; STARCH, CORN; CORN SYRUP; STARCH, WHEAT; ETHYL ACETATE; FD&C BLUE NO. 1 ALUMINUM LAKE; FD&C BLUE NO. 2 ALUMINUM LAKE; FD&C RED NO. 40; FD&C RED NO. 40 ALUMINUM LAKE; FD&C YELLOW NO. 5 ALUMINUM LAKE; FD&C YELLOW NO. 6; FD&C YELLOW NO. 6 ALUMINUM LAKE; ISOPROPYL ALCOHOL; MALTODEXTRIN; METHYLPARABEN; MODIFIED CORN STARCH (1-OCTENYL SUCCINIC ANHYDRIDE); BUTYL ALCOHOL; PHOSPHORIC ACID; POVIDONE, UNSPECIFIED; PROPYLENE GLYCOL; PROPYLPARABEN; WATER; SHELLAC; SODIUM BENZOATE; SORBIC ACID; SORBITOL; SOYBEAN; SOYBEAN LECITHIN; SUCROSE; TERT-BUTYLHYDROQUINONE; TITANIUM DIOXIDE; TRIACETIN; CORN OIL

Drug Facts

Active ingredient (per tablet)

Calcium Carbonate USP 750mg

Purpose

Antacid

Uses

relieves

- heartburn
- acid indigestion
- sour stomach
- upset stomach associated with these symptoms

Warnings

Ask a doctor or pharmacist before use if you are

presently taking a prescription drug. Antacids may interact with certain prescription drugs.

When using this product

- do not take more than 6 tablets in 24 hours
- if pregnant do not take more than 6 tablets in 24 hours
- do not use the maximum dosage for more than 2 weeks, except under the advice and supervision of a doctor

Directions

- adults and children 12 years of age and over:chew 2-4 tablets as symptoms occur, or as directed by a doctor. Crush or chew tablets completely before swallowing.
- do not take for symptoms that persist for more than 2 weeks unless advised by a doctor

Other Information

- each chewable tablet contains:elemental calcium 300mg
- do not store above 25°C (77°F)
- contains FD&C Yellow No. 5 (tartrazine) as a color additive

Inactive ingredients

acacia, beeswax, carmine, carnauba wax, citric acid, coconut oil, corn starch, corn syrup, dextrin, FD&C blue no. 2 aluminum lake, FD&C red no. 40, FD&C red no. 40 aluminum lake, FD&C yellow no. 5 aluminum lake (tartrazine), maltodextrin, medium chain triglycerides, methylparaben, natural and artificial flavors, pharmaceutical ink, phosphoric acid, povidone, propylene glycol, propylparaben, purified water, shellac, sodium benzoate, sorbic acid, sorbitol, soy lecithin, sucrose, titanium dioxide, triacetin, vegetable oil

Questions or comments?

1-800-897-7535

Generic Section (2 ct. Pouch)

Extra Stregnth 750

TUMS ANTACID

Chewy Bites

Assorted Berries

20 Packets of 2 TABLETS